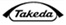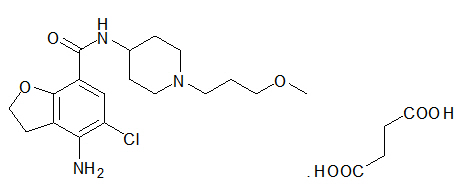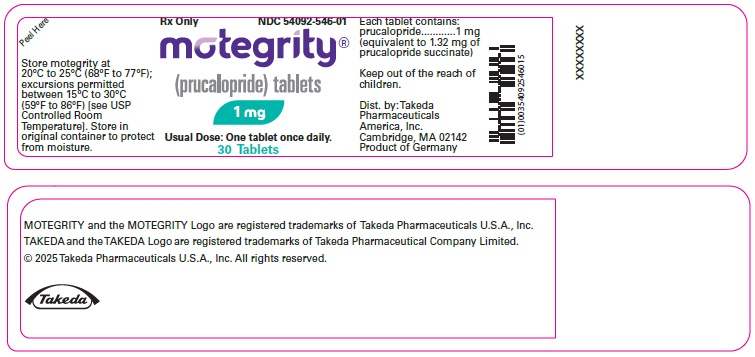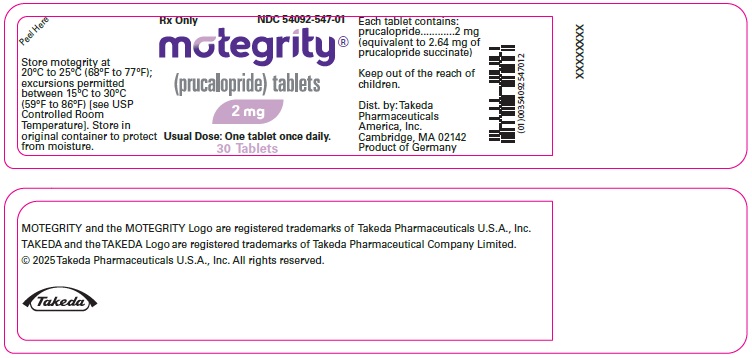 DRUG LABEL: MOTEGRITY
NDC: 54092-546 | Form: TABLET, FILM COATED
Manufacturer: Takeda Pharmaceuticals America, Inc.
Category: prescription | Type: HUMAN PRESCRIPTION DRUG LABEL
Date: 20250717

ACTIVE INGREDIENTS: PRUCALOPRIDE SUCCINATE 1 mg/1 1
INACTIVE INGREDIENTS: LACTOSE MONOHYDRATE; MICROCRYSTALLINE CELLULOSE; SILICON DIOXIDE; MAGNESIUM STEARATE; HYPROMELLOSE 2910 (6 MPA.S); TRIACETIN; TITANIUM DIOXIDE; POLYETHYLENE GLYCOL 3000

HIGHLIGHTS OF PRESCRIBING INFORMATION

These highlights do not include all the information needed to use MOTEGRITY® safely and effectively. See full prescribing information for MOTEGRITY.
MOTEGRITY (prucalopride) tablets, for oral use
Initial U.S. Approval: 2018

1 INDICATIONS AND USAGE

MOTEGRITY is a serotonin-4 (5-HT4) receptor agonist indicated for the treatment of chronic idiopathic constipation (CIC) in adults. (1)

2 DOSAGE AND ADMINISTRATION

- Take with or without food. (2)
- Recommended dosage by patient population:

Population with CIC | Recommended Oral Dose Regimen
Adults | 2 mg once daily. (2)
Patients with severe renal impairment (creatinine clearance (CrCL) less than 30 mL/min) | 1 mg once daily. (2, 8.5, 8.6)

3 DOSAGE FORMS AND STRENGTHS

Tablets: 1 mg, 2 mg of prucalopride. (3)

4 CONTRAINDICATIONS

- Hypersensitivity to MOTEGRITY. (4)
- Intestinal perforation or obstruction due to structural or functional disorder of the gut wall, obstructive ileus, severe inflammatory conditions of the intestinal tract such as Crohn's disease, ulcerative colitis, and toxic megacolon/megarectum. (4)

5 WARNINGS AND PRECAUTIONS

Suicidal Ideation and Behavior: Monitor patients for suicidal ideation and behavior as well as self-injurious ideation and new-onset or worsening of depression. Instruct patients to discontinue MOTEGRITY immediately and contact their healthcare provider if they experience any unusual changes in mood or behavior, or they experience emerging suicidal thoughts or behaviors. (5.1)

6 ADVERSE REACTIONS

Most common adverse reactions (≥2%) are headache, abdominal pain, nausea, diarrhea, abdominal distension, dizziness, vomiting, flatulence, and fatigue. (6.1)

To report SUSPECTED ADVERSE REACTIONS, contact Takeda Pharmaceuticals at 1-800-828-2088 or FDA at 1-800-FDA-1088 or www.fda.gov/medwatch.

FULL PRESCRIBING INFORMATION

1 INDICATIONS AND USAGE

MOTEGRITY® is indicated for the treatment of chronic idiopathic constipation (CIC) in adults.

2 DOSAGE AND ADMINISTRATION

MOTEGRITY can be taken with or without food. The recommended dosage by patient population is shown in Table 1.

Table 1: Recommended Dosage Regimen and Dosage Adjustments by Population
Population with CIC | Recommended Oral Dose Regimen
Adults | 2 mg once daily
Patients with severe renal impairment (creatinine clearance (CrCL) less than 30 mL/min) [see Use in Specific Populations (8.5, 8.6)]. | 1 mg once daily

3 DOSAGE FORMS AND STRENGTHS

MOTEGRITY Tablets:

- 1 mg prucalopride: White to off-white, round, biconvex film-coated tablet debossed with "PRU 1" on one side and no debossing on the other side.
- 2 mg prucalopride: Pink, round, biconvex film-coated tablet debossed with "PRU 2" on one side and no debossing on the other side.

4 CONTRAINDICATIONS

MOTEGRITY is contraindicated in patients with:

- A history of hypersensitivity to MOTEGRITY. Reactions including dyspnea, rash, pruritus, urticaria, and facial edema have been observed [see Adverse Reactions (6.2)].
- Intestinal perforation or obstruction due to structural or functional disorder of the gut wall, obstructive ileus, severe inflammatory conditions of the intestinal tract such as Crohn's disease, ulcerative colitis, and toxic megacolon/megarectum.

5 WARNINGS AND PRECAUTIONS

5.1 Suicidal Ideation and Behavior

In clinical trials, suicides, suicide attempts, and suicidal ideation have been reported. Postmarketing cases of suicidal ideation and behavior as well as self-injurious ideation and new onset or worsening of depression have been reported within the first few weeks of starting MOTEGRITY [see Adverse Reactions (6.1, 6.2)].

A causal association between treatment with MOTEGRITY and an increased risk of suicidal ideation and behavior has not been established.

Monitor all patients treated with MOTEGRITY for new onset or worsening of depression or the emergence of suicidal thoughts and behaviors. Counsel patients, their caregivers, and family members of patients to be aware of any unusual changes in mood or behavior and alert the healthcare provider. Instruct patients to discontinue MOTEGRITY immediately and contact their healthcare provider if they experience any of these symptoms.

6 ADVERSE REACTIONS

6.1 Clinical Trials Experience

Because clinical trials are conducted under widely varying conditions, adverse reaction rates observed in the clinical trials of a drug cannot be directly compared to rates in the clinical trials of another drug and may not reflect the rates observed in practice.

The data described below represent 2,530 patients (1,251 received MOTEGRITY 2 mg once daily and 1,279 received placebo) with CIC from 6 double-blind, placebo-controlled clinical trials of 12 weeks to 24 weeks in duration. In these trials overall, patients were primarily female (76%) and white (76%). The mean age was 47 years (range 17 to 95 years) [see Clinical Studies (14)].

Common Adverse Reactions

Table 2 below summarizes the incidence (%) of common adverse reactions occurring in at least 2% of patients with CIC receiving either 2 mg of MOTEGRITY once daily or placebo and at an incidence greater than in the placebo group from the six double-blind placebo-controlled trials described above.

Table 2: Common Adverse Reactions [Reported in ≥2% of patients receiving MOTEGRITY and a rate higher than patients receiving placebo.] in Double-Blind Placebo-Controlled Trials of CIC of at least 12 Weeks Duration
Adverse Reaction | MOTEGRITY 2 mg Once Daily N=1,251 [Includes 93 patients who started on MOTEGRITY 1 mg and increased to MOTEGRITY 2 mg.] % | Placebo N=1,279 %
Headache | 19 | 9
Abdominal pain [Includes abdominal pain, upper abdominal pain, lower abdominal pain, abdominal tenderness, abdominal discomfort, and epigastric discomfort.] | 16 | 11
Nausea | 14 | 7
Diarrhea | 13 | 5
Abdominal distension | 5 | 4
Dizziness | 4 | 2
Vomiting | 3 | 2
Flatulence | 3 | 2
Fatigue | 2 | 1

Less Common Adverse Reactions

Less common adverse reactions occurring in <2% of patients receiving MOTEGRITY 2 mg once daily include:

Gastrointestinal disorders: Abnormal gastrointestinal sounds

Metabolism and nutrition disorders: Decreased appetite

Nervous system disorders: Migraine

Renal and urinary disorders: Pollakiuria

Diarrhea

Of the patients who reported diarrhea, 70% (110 out of 157) reported it in the first week of treatment. Diarrhea typically resolved within a few days in 73% (80 out of 110) of those patients. Severe diarrhea was reported in 1.8% of patients treated with MOTEGRITY 2 mg compared to 1% of patients in the placebo group, and had a similar onset and duration as diarrhea overall.

Headache

Of the patients who reported headache, 66% (157 out of 237) treated with MOTEGRITY 2 mg once daily reported onset in the first 2 days of treatment. Symptoms typically resolved within a few days in 65% (102 out of 157) of those patients.

Adverse Reactions Leading to Discontinuation

In the 6 clinical trials described above, 5% of patients treated with 2 mg of MOTEGRITY once daily discontinued due to adverse reactions, compared to 3% of patients in the placebo group. The most common adverse reactions leading to discontinuation were nausea (2% MOTEGRITY, 1% placebo), headache (1% MOTEGRITY, 1% placebo), diarrhea (1% MOTEGRITY, <1% placebo), or abdominal pain (1% MOTEGRITY, 1% placebo).

Adverse Reactions of Special Interest

Adverse reactions of special interest were evaluated in a pool of 28 completed clinical trials (19 double-blind and 9 open-label) for MOTEGRITY at doses including 0.5 mg, 1 mg, 2 mg, or 4 mg per day in adult patients with CIC (the recommended dosage of MOTEGRITY for CIC is 2 mg once daily). The total exposure in the double-blind trials was 565 patient-years in the MOTEGRITY group, 384 patient-years in the placebo group, and 2,769 patient-years in the double-blind and open-label clinical trials.

Cardiovascular Safety Analysis

In an evaluation by an independent adjudication committee of all potential major adverse cardiovascular events (MACE), defined as cardiovascular death, nonfatal myocardial infarction, and nonfatal stroke, the standardized incidence rate (IR) per 1,000 patient-years for MACE for MOTEGRITY was compared with the IR for placebo.

In the double-blind trials, the IR for MACE was 3.5 (2 patients out of 3,366; 1 patient on 2 mg and 1 patient on 4 mg) in the MOTEGRITY group and 5.2 (2 patients out of 2,019) in the placebo group. When combining the double-blind and open-label trials, the IR for MACE was 3.3 (9 patients out of 4,472, doses ranging between 0.5 to 4 mg) for MOTEGRITY.

Suicidal Ideation and Behavior

In the double-blind trials, one patient reported a suicide attempt 7 days after the end of treatment with MOTEGRITY 2 mg once daily; none were reported in patients on placebo. In the open-label trials, two patients reported a suicide attempt and another patient reported suicidal ideation. Completed suicide was reported in two patients, previously treated with MOTEGRITY 2 mg or 4 mg; both discontinued MOTEGRITY for at least one month prior to the event.

Observational Cardiovascular Cohort Study

The overall cardiovascular safety of MOTEGRITY was assessed using European healthcare databases in a population-based, retrospective, observational, cohort study of adults with constipation. New users of MOTEGRITY (N=5,715) were matched to new users of polyethylene glycol 3350 (PEG) (N=29,372) to estimate the standardized incidence rate ratio (SIRR) for MACE, pooled across four data sources. The 95% confidence interval for the pooled estimate of the SIRR did not demonstrate an increased MACE risk and excluded a pre-specified safety margin of a three-fold risk of MACE during prucalopride use relative to PEG use.

6.2 Postmarketing Experience

The following adverse reactions have been identified during post-approval use of MOTEGRITY (prucalopride). Because these reactions are reported voluntarily from a population of uncertain size, it is not always possible to reliably estimate their frequency or establish a causal relationship to drug exposure.

Hypersensitivity reactions: Dyspnea, rash, pruritus, urticaria, and facial edema [see Contraindications (4)].

Psychiatric disorders: Suicide, suicide attempts, suicidal ideation, self-injurious ideation, depression, anxiety, insomnia, nightmares, and visual hallucinations [see Warnings and Precautions (5.1)].

8 USE IN SPECIFIC POPULATIONS

8.1 Pregnancy

Pregnancy Exposure Registry

There is a pregnancy exposure registry that monitors pregnancy outcomes in women exposed to MOTEGRITY during pregnancy. Healthcare providers are encouraged to register patients by contacting MotherToBaby Pregnancy Studies conducted by the Organization of Teratology Information Specialists (OTIS) at 1-877-311-8972 or visiting https://mothertobaby.org/pregnancy-studies/.

Risk Summary

Available data from case reports with prucalopride use in pregnant women are insufficient to identify any drug-associated risks of miscarriage, major birth defects, or adverse maternal or fetal outcomes. In animal reproduction studies, no adverse developmental effects were observed with prucalopride administration during the period of organogenesis to pregnant rats and rabbits at doses up to approximately 390 times and 780 times, respectively, the recommended human dose of 2 mg/day (see Data).

The estimated background risk of major birth defects and miscarriage for the indicated population is unknown. All pregnancies have a background risk of birth defect, loss, or other adverse outcomes. In the U.S. general population, the estimated background risk of major birth defects and miscarriage in clinically recognized pregnancies is 2 to 4% and 15 to 20%, respectively.

Data

Animal Data

In oral embryofetal development studies in rats and rabbits, prucalopride was administered to pregnant animals at doses of 5, 20, and 80 mg/kg/day throughout the period of organogenesis. No adverse embryofetal developmental effects were observed in either rats or rabbits up to the highest oral dose of 80 mg/kg/day (about 390 times and 780 times the recommended human dose of 2 mg/day, respectively, based on body surface area).

In an oral pre- and post-natal development study in rats, prucalopride was administered at doses of 5, 20, and 80 mg/kg/day. At the 80-mg/kg dose (about 390 times the recommended human dose of 2 mg/day, based on body surface area), a slight decrease in overall survival rate of pups after 7 days was observed, which could be due to maternal toxicity observed at this dose.

8.2 Lactation

Risk Summary

Prucalopride is present in breast milk (see Data). There are no data on the effects of prucalopride on the breastfed child or the effects on milk production. The developmental and health benefits of breastfeeding should be considered along with the mother's clinical need for MOTEGRITY and any potential adverse effects on the breastfed child from MOTEGRITY or from the underlying maternal condition.

Data

In an open-label study in 8 healthy lactating women in the weaning stage, plasma and milk samples were collected at predose (day 1 and 4), and then 2, 4, 8, 12, and 24 hours (day 4) after a 2-mg dose of prucalopride was administered once daily for 4 days. Prucalopride is excreted in breast milk with a milk to plasma AUC ratio of 2.65:1; the average amount passed to the infant was estimated to be 1.74 mcg/kg/day, which is about 6% of the maternal dose, adjusted for body weight. The prucalopride concentration detected in breast milk during weaning may not reflect the prucalopride concentration in breast milk during full milk production.

8.4 Pediatric Use

The safety and effectiveness of MOTEGRITY have not been established in pediatric patients. MOTEGRITY was evaluated in a 12-week randomized, double-blind, placebo-controlled study, followed by a 36-week double-blind extension study in patients 6 months to 17 years with functional constipation. The interim analysis of the primary endpoint showed that the number of spontaneous bowel movements per week over 12 weeks was similar between the MOTEGRITY and placebo groups, indicating that the study was unlikely to demonstrate effectiveness. Therefore, the study was terminated early for futility. Adverse reactions reported in pediatric patients in this study were similar to those reported in adults.

8.5 Geriatric Use

Of the 2,484 patients treated with MOTEGRITY 1 mg or 2 mg once daily in 6 controlled trials of at least 12-week duration in patients with CIC, 15% were 65 years of age and over, and 5% were 75 years of age and over [see Clinical Studies (14)]. No overall differences in safety and effectiveness were observed between elderly and younger patients.

In an additional 4-week double-blind, placebo-controlled dose escalation study in 89 elderly nursing home residents with CIC (PRU-USA-26, NCT00627692), no unanticipated safety issues were identified.

Elderly subjects had higher prucalopride exposure compared to younger subjects. However, the effect of age on the pharmacokinetics of prucalopride appeared to be related to decreased renal function [see Clinical Pharmacology (12.3)]. Adjust the dosage in elderly patients based on renal function [see Dosage and Administration (2), Use in Specific Populations (8.6)].

8.6 Renal Impairment

No dosage adjustment is required for patients with mild and moderate renal impairment (creatinine clearance at least 30 mL/min, as determined from a 24-hour urine collection in the clinical trial).

MOTEGRITY is known to be substantially excreted by the kidney, and the risk of adverse reactions may be greater in patients with impaired renal function. A decreased dosage is recommended in patients with severe renal impairment (creatinine clearance less than 30 mL/min, as determined from a 24-hour urine collection in the clinical trial) [see Dosage and Administration (2)].

Avoid MOTEGRITY in patients with end-stage renal disease requiring dialysis [see Clinical Pharmacology (12.3)].

10 OVERDOSAGE

An overdose may result in appearance of symptoms from an exaggeration of the known pharmacodynamic effects of prucalopride and includes headache, nausea, and diarrhea. Specific treatment is not available for MOTEGRITY overdose. Should an overdose occur, treat symptomatically and institute supportive measures, as required. Extensive fluid loss from diarrhea or vomiting may require correction of electrolyte disturbances.

11 DESCRIPTION

MOTEGRITY (prucalopride) tablets for oral use contain prucalopride succinate, a dihydrobenzofurancarboxamide that is a serotonin type 4 (5-HT4) receptor agonist. The IUPAC name is: 4-amino-5-chloro-N-[1-(3-methoxypropyl)piperidin-4-yl]-2,3-dihydrobenzofuran-7-carboxamide succinate.

The molecular formula is C18H26ClN3O3.C4H6O4 and the molecular weight is 485.96. The structural formula is:

Prucalopride succinate is a white to almost white powder. It is highly soluble in acidic aqueous media and alkaline aqueous media up to a pH of approximately 9.

Each 1-mg film-coated tablet of MOTEGRITY contains 1 mg of prucalopride (equivalent to 1.32 mg prucalopride succinate), and the following inactive ingredients: colloidal silicon dioxide, lactose monohydrate, magnesium stearate, and microcrystalline cellulose. The coating for the 1-mg tablet contains hypromellose, lactose monohydrate, polyethylene glycol 3000, titanium dioxide, and triacetin.

Each 2-mg film-coated tablet of MOTEGRITY contains 2 mg of prucalopride (equivalent to 2.64 mg prucalopride succinate), and the following inactive ingredients: colloidal silicon dioxide, lactose monohydrate, magnesium stearate, and microcrystalline cellulose. The coating for the 2-mg tablet contains hypromellose, lactose monohydrate, polyethylene glycol 3000, titanium dioxide, triacetin, red iron oxide, yellow iron oxide, and FD&C Blue #2.

12 CLINICAL PHARMACOLOGY

12.1 Mechanism of Action

Prucalopride, a selective serotonin type 4 (5-HT4) receptor agonist, is a gastrointestinal (GI) prokinetic agent that stimulates colonic peristalsis (high-amplitude propagating contractions [HAPCs]), which increases bowel motility.

Prucalopride was devoid of effects mediated via 5-HT2A, 5-HT2B, 5-HT3, motilin or CCK-A receptors in vitro at concentrations exceeding 5-HT4 receptor affinity by 150-fold or greater. In isolated GI tissues from various animal species, prucalopride facilitated acetylcholine release to enhance the amplitude of contractions and stimulate peristalsis. In rats and dogs, prucalopride stimulated gastrointestinal motility with contractions starting from the proximal colon to the anal sphincter.

12.2 Pharmacodynamics

High Amplitude Propagating Contractions

Following a single 2-mg dose of prucalopride in patients with CIC, prucalopride increased the number of high amplitude propagating contractions (HAPCs) during the first 12 hours as compared with an osmotic laxative treatment. In addition, prucalopride 4 mg once daily (2 times the maximum human recommended dose of 2 mg) for 7 days increased the amplitude of HAPCs in healthy subjects without affecting colonic phasic activity as compared with placebo.

Colonic Transit Time

An integrated analysis of 3 randomized, placebo-controlled, dose-finding studies in 280 patients with CIC showed that after once daily treatment with 2 mg of prucalopride, the mean colonic transit time was reduced by 12 hours from a baseline of 65 hours for prucalopride 2 mg, compared to an increase of 0.5 hours from a baseline of 66 hours in the placebo group.

Cardiac Electrophysiology

At a dose 5 times the maximum approved recommended dose, MOTEGRITY does not prolong the QT interval to any clinically relevant extent.

12.3 Pharmacokinetics

The pharmacokinetics of prucalopride has been evaluated in healthy subjects and is dose-proportional within and beyond the therapeutic range (tested up to 20 mg, 10 times the maximum approved recommended dose). Prucalopride administered once daily displays time-independent kinetics during prolonged treatment. With once daily administration of 2 mg prucalopride, pharmacokinetic steady-state is attained within 3 to 4 days, and steady-state plasma concentrations fluctuate between trough and peak values of 2.5 and 7 ng/mL, respectively, with mean plasma AUC0-24h of 109 ng∙h/mL. The accumulation ratio after once daily dosing ranged from 1.9 to 2.3. The terminal half-life is approximately 1 day.

Pharmacokinetic parameters in patients with CIC are similar to those seen in healthy subjects.

Absorption

Following a single oral dose of 2 mg prucalopride in healthy subjects, peak plasma concentrations are observed within 2 to 3 hours after administration. The absolute oral bioavailability is >90%.

Effect of Food

Concomitant intake with a high-fat meal (1,000 kcal total, 500 kcal from fat) does not influence the oral bioavailability of prucalopride [see Dosage and Administration (2)].

Distribution

Prucalopride has a steady-state volume of distribution (Vss) of 567 liters after intravenous administration. The plasma protein binding of prucalopride is approximately 30%.

Elimination

Renal excretion is the main route of elimination of prucalopride. Non-renal elimination contributes up to about 35% of the total. The plasma clearance of prucalopride averages 317 mL/min.

Metabolism

Prucalopride is a substrate of CYP3A4, in vitro. In an oral dose study with radiolabeled prucalopride in healthy subjects, prucalopride made up 92 to 94% of the total radioactivity in plasma. There are 7 different known minor metabolites, the most abundant metabolite (O-desmethyl prucalopride acid) represents 0 to 1.7% of the total plasma exposure.

Excretion

Following oral administration of radiolabeled prucalopride in healthy subjects, 60 to 65% of the administered dose is excreted unchanged in urine and about 5% in feces. On average, 84.2% of administered radioactive dose was recovered in urine and 13.3% of the dose was recovered in feces. Seven metabolites were recovered in urine and feces, with the most abundant metabolite (O-desmethyl prucalopride acid) accounting for 3.2% and 3.1% of the dose in urine and feces, respectively. None of the other metabolites accounted for more than 3% of the dose. Renal elimination of prucalopride involves both passive filtration and active secretion.

Use in Specific Populations

Population pharmacokinetic analysis of a combined study population of 1,343 subjects indicated that there were no clinically significant differences in the pharmacokinetics of prucalopride based on age (17-95 years), sex, race (89% white, 7% black, 4% other), or body weight (37-161 kg), after accounting for the effect of renal function.

Geriatric Patients

After once daily dosing of 1 mg, peak plasma concentrations (Cmax) and AUC of prucalopride in geriatric subjects were 26% to 28% higher than in younger adult subjects. The effect of age appeared to be related to decreased renal function in the elderly. Additionally, a population pharmacokinetic analysis indicated that age was not a significant covariate, after accounting for the effect of renal function [see Use in Specific Populations (8.5)].

Patients with Renal Impairment

After a single 2-mg oral dose, the mean AUC0-inf of prucalopride increased 1.23-fold in subjects with mild renal impairment (creatinine clearance 60 to ≤89 mL/min), 1.4-fold in subjects with moderate renal impairment (creatinine clearance 30 to ≤59 mL/min), and 2.38-fold in subjects with severe renal impairment (creatinine clearance 15 to ≤29 mL/min), compared to subjects with normal renal function. The pharmacokinetics of prucalopride in patients with end-stage renal disease or undergoing dialysis is not fully known [see Dosage and Administration (2), Use in Specific Populations (8.6)].

Patients with Hepatic Impairment

After a single oral dose of 2 mg, Cmax and AUC of prucalopride were on average 10 to 20% higher in subjects with moderate (Child-Pugh B) and severe (Child-Pugh C) hepatic impairment than in subjects with normal hepatic function. This effect is not considered to be clinically significant.

Drug Interaction Studies

Clinical Studies

Effect of Prucalopride on Other Drugs

Erythromycin

Coadministration of oral erythromycin (500 mg four times daily) with prucalopride increased the erythromycin mean Cmax by 40% and mean AUC0-24h by 28%. The mechanism for this interaction is not clear. The increased exposure to erythromycin is unlikely to be clinically significant.

Other Drugs

No clinically significant differences in the pharmacokinetics (no more than a 10% change in AUC) of the following drugs were observed when coadministered with prucalopride: warfarin, digoxin, paroxetine, or oral contraceptives (ethinyl estradiol and norethisterone).

Effect of Other Drugs on Prucalopride

Ketoconazole

Ketoconazole (200 mg twice daily), a strong CYP3A inhibitor and inhibitor of P-gp and BCRP, increased the Cmax and AUC of prucalopride by approximately 40%. This effect is unlikely to be clinically significant.

Other Drugs

No clinically significant differences in prucalopride pharmacokinetics (no more than a 10% change in AUC) were observed when coadministered with erythromycin, probenecid, cimetidine, or paroxetine.

In Vitro Studies

Based on in vitro study results, the potential for prucalopride to inhibit CYP enzymes (1A2, 2A6, 2B6, 2C8, 2C9, 2C19, 2D6, 2E1, and 3A4) and transporters (P-gp, BCRP, OATP1B1, OATP1B3, OAT1, OAT3, OCT1, OCT2, MATE1, MATE2-K, BSEP, and MRP2 transporters) or induce CYP enzymes (1A2, 2B6, and 3A4) is low at the clinical concentration.

13 NONCLINICAL TOXICOLOGY

13.1 Carcinogenesis, Mutagenesis, Impairment of Fertility

Carcinogenesis

In a 2-year carcinogenicity study in mice, prucalopride was given by daily oral gavage at doses of 10, 20, and 80 mg/kg. An increased incidence of mammary gland adenocarcinomas was observed in female mice at 80 mg/kg/day. The finding is considered rodent-specific. No significant neoplastic changes were seen in male mice dosed up to 80 mg/kg/day and in female mice dosed up to 20 mg/kg/day (exposure ratio of 219 and 24 times the human dosage of 2 mg per day in male and female mice, respectively, based on AUC).

In a 2-year carcinogenicity study in rats, prucalopride was given by daily oral gavage at doses of 5, 20, and 80 mg/kg in males and 5, 10, and 40 mg/kg in females. In male and female rats there was a significant increase in the incidences of benign tumors, including hepatocellular adenomas, thyroid follicular adenomas, and mammary gland fibroadenomas. An increased incidence of pituitary adenomas, pancreas islet cell adenomas, and adrenal gland benign pheochromocytomas was also seen in male rats. The increases in neoplastic changes occurred primarily at the high dose of 80 mg/kg/day in male rats and 40 mg/kg/day in female rats (exposure ratios 556 times (males) and 495 times (females) the human dosage of 2 mg per day, based on AUC). There was no significant increase in tumor incidence at doses up to 20 mg/kg/day in male rats and up to 10 mg/kg/day in female rats (exposure ratios of 63 and 40 times the human dosage of 2 mg per day in male and female rats, respectively, based on AUC).

In a 12-month carcinogenicity study in neonatal mice, prucalopride was administered by oral gavage at total dosages of 75, 150, and 300 mg/kg given across 2 doses on day 8 of age (one-third of total dosage) and day 15 of age (two-thirds of total dosage). Prucalopride was not tumorigenic at doses up to 300 mg/kg (>1,600 times the human exposure at 2 mg per day, based on AUC).

Mechanistic studies demonstrated that the increase in tumor incidence in rodents related to stimulation of prolactin in endocrine tissues was associated with dopamine D2 antagonist activity. The hepatic and thyroid tumors were due to induction of enzymes in liver and subsequent disruption of thyroid homeostasis.

Mutagenesis

Prucalopride was tested in a battery of assays, including the Ames bacterial mutation assay in Salmonella typhimurium and Escherichia coli, mouse lymphoma assay, chromosomal aberration assays in human lymphocytes, micronucleus test in mice, Vitotox test, and in vitro Unscheduled DNA Synthesis (UDS) studies. Prucalopride tested positive in the Ames bacterial mutation assay in the S. typhimurium TA100 strain, at concentrations ≥500 mcg/plate, both in the presence and absence of metabolic activation. Prucalopride was negative in other assays evaluating mutagenesis, including in vitro mammalian-based assays (e.g., mouse lymphoma assay, chromosomal aberration assays in human lymphocytes) and in vivo tests (e.g., micronucleus test in mice, a UDS test, a gene mutation assay in Big Blue transgenic rats, and a ^32P-postlabeling study in target tissues identified in the carcinogenicity studies, including liver, mammary gland, thyroid, and adrenal tissues). Based on the weight of evidence, prucalopride does not appear to have a mutagenic potential.

Impairment of Fertility

In an oral fertility and early embryonic development study performed in rats at doses of 5, 20, and 80 mg/kg/day, there was no evidence of adverse effects on fertility at doses up to 20 mg/kg. At the highest dose of 80 mg/kg (about 390 times the recommended human dose of 2 mg/day, based on body surface area), an increase in pre-coital interval, pseudo-pregnancies, and pre-implantation loss were seen. These effects could be secondary to increased prolactin secretion with prucalopride treatment.

13.2 Animal Toxicology and/or Pharmacology

In safety pharmacology studies, no relevant effects were observed in any of the cardiovascular studies at concentrations at least 50 times the human therapeutic Cmax. Prucalopride had no effect on potassium current in hERG-transfected HEK cells at concentrations up to 1 micromolar (50 times the human therapeutic Cmax). At concentrations ≥3 micromolar, concentration-dependent inhibition of the current was observed (IC50=22 micromolar; 1,100 times the human therapeutic Cmax). In studies in pigs, minor and transient increases in heart rate and blood pressure were noted upon first exposure to prucalopride, at plasma levels at least 10 times the human therapeutic Cmax.

In repeated-dose toxicology studies in male rats, increases in heart weight (up to 9%) were observed at doses of 20 mg/kg/day or higher (at least 75 times the human therapeutic AUC). Cardiac histology revealed an increase in focal infiltration of chronic inflammatory cells in the heart at a dose of 80 mg/kg/day (at least 785 times the human therapeutic AUC). In dogs, no changes in heart rate, blood pressure, electrocardiogram parameters, heart weight, or cardiac histology were observed at any dose tested (the highest dose of 30 mg/kg/day was 572 times the human therapeutic AUC).

In vitro studies demonstrated no effect of prucalopride on either contractile responses in human, canine, and porcine coronary arteries at concentrations up to 10 micromolar (500 times the human clinical Cmax) or on platelet aggregation at concentrations up to 200 nanomolar (10 times the human clinical Cmax).

14 CLINICAL STUDIES

The efficacy of MOTEGRITY for the treatment of CIC was evaluated in six double-blind, placebo-controlled, randomized, multicenter clinical trials in 2,484 adult patients (Studies 1 to 6; see Table 3). Studies 1 through 5 were 12-week treatment duration and Study 6 included 24 weeks of treatment. Patients less than 65 years were dosed with MOTEGRITY 2 mg once daily. In Studies 2 and 6, the geriatric patients started on MOTEGRITY 1 mg once daily and, if necessary, the dose was increased to 2 mg after 2 or 4 weeks of treatment in the event of insufficient response at 1 mg; of these patients 81% increased to 2 mg. Overall, the majority of patients were female (76%) and white (76%), and also included Asian (19%) and black (3%). The mean adult age was 47±16 years (range 17 to 95 years) and the mean duration of constipation was 16±15 years with 28% of patients having chronic constipation for at least 20 years.

Table 3: Main Studies in the MOTEGRITY Clinical Program
Study Number | Duration
Study 1 (PRU-CRC-3001, NCT01116206) | 12 Weeks
Study 2 (SPD555-302, NCT01147926) | 12 Weeks
Study 3 (PRU-INT-6, NCT00488137) | 12 Weeks
Study 4 (PRU-USA-11, NCT00483886) | 12 Weeks
Study 5 (PRU-USA-13, NCT00485940) | 12 Weeks
Study 6 (SPD-555-401, NCT01424228) | 24 Weeks

Eligible patients required a history of chronic constipation defined as having fewer than 3 spontaneous bowel movements (SBMs) per week that resulted in a feeling of complete evacuation (complete, spontaneous bowel movement [CSBM]) and 1 or more of the following symptoms for greater than 25% of bowel movements in the preceding 3 months, with symptoms onset more than 6 months prior to screening:

- Lumpy or hard stools
- Sensation of incomplete evacuation
- Straining at defecation

Patients who never had SBMs were eligible. In Study 1, eligibility also included sensation of ano-rectal obstruction or blockade or the need for digital manipulation in more than 25% of bowel movements. In all studies, patients were excluded if constipation was due to secondary causes or suspected to be drug-induced.

Efficacy was assessed using information provided by patients in a daily diary.

Primary Efficacy Results

For the primary efficacy endpoint, a responder was defined as a patient with an average of 3 or more CSBMs per week, over the 12-week treatment period. In the Intent-to-Treat [ITT] population in the 6 trials, 1,237 received MOTEGRITY 1 or 2 mg and 1,247 received placebo. Table 4 summarizes the results.

Table 4: Efficacy Responder Rates in Placebo-Controlled Studies of CIC: Proportion of Patients with an Average Weekly Frequency of ≥3 CSBMs per Week over 12 Weeks of Treatment (ITT Population)
Study | MOTEGRITY 1 or 2 mg Once Daily |  | Placebo |  | Treatment Difference (95% CI) | p value
 | N | n (%) | N | n (%)
Study 1 | 249 | 83 (33) | 252 | 26 (10) | 23 (16, 30) | p<0.001
Study 2 | 177 | 67 (38) | 181 | 32 (18) | 20 (11, 29) | p<0.001
Study 3 | 236 | 46 (19) | 240 | 23 (10) | 10 (4, 16) | p=0.002
Study 4 | 190 | 55 (29) | 193 | 25 (13) | 16 (8, 24) | p<0.001
Study 5 | 214 | 50 (24) | 212 | 25 (12) | 12 (4, 19) | p<0.001
Study 6 | 171 | 43 (25) | 169 | 34 (20) | 5 (-4, 14) | p=0.341
p-value based on a Cochran-Mantel-Haenszel test
N = number of patients per treatment group
n = number of responders

In all studies, improvement in the frequency of CSBMs/week was seen as early as week 1 and was maintained through week 12.

Across the six studies, the median time to first CSBM after dosing of MOTEGRITY on day 1 ranged from 1.4 to 4.7 days compared with 9.1 to 20.6 days in the placebo group. The median time to first SBM after dosing on day 1 ranged from 0.1 to 0.4 days in the MOTEGRITY group compared with 1.0 to 1.6 days in the placebo group.

Alternative Efficacy Endpoint

Using an alternative efficacy endpoint, a responder was defined as a patient who had at least 3 CSBMs and an increase of at least 1 CSBM from baseline in a given week for at least 9 weeks out of the 12-week treatment period and for at least 3 of the last 4 weeks of the treatment period. The differences in response rates between MOTEGRITY and placebo in the 6 studies are shown in Table 5.

Table 5: Efficacy Responder Rates in Placebo-Controlled Studies of CIC - Proportion of Patients with an Average of ≥3 CSBMs/week and an Increase of ≥1 CSBM per Week for at Least 9 out of the 12 Weeks, Including 3 of the Last 4 Weeks (ITT Population)
Study | MOTEGRITY 1 or 2 mg Once Daily |  | Placebo |  | Treatment Difference (95% CI)
 | N | n (%) | N | n (%)
Study 1 | 249 | 65 (26) | 252 | 22 (9) | 17 (11, 24)
Study 2 | 177 | 57 (32) | 181 | 25 (14) | 18 (10, 27)
Study 3 | 236 | 30 (13) | 240 | 13 (5) | 8 (2, 12)
Study 4 | 190 | 37 (19) | 193 | 15 (8) | 11 (5, 18)
Study 5 | 214 | 34 (16) | 212 | 11 (5) | 11 (5, 16)
Study 6 | 171 | 29 (17) | 169 | 22 (13) | 4 (-4, 12)
CSBM = complete spontaneous bowel movement
N = number of patients per treatment group
n = number of responders

16 HOW SUPPLIED/STORAGE AND HANDLING

MOTEGRITY tablets containing 1 mg prucalopride are white to off-white, round, biconvex film-coated tablets debossed with "PRU 1" on one side and no debossing on the other side. They are supplied as:

- NDC 54092-546-01: HDPE bottle of 30 tablets, with child-resistant closure.

MOTEGRITY tablets containing 2 mg prucalopride are pink, round, biconvex film-coated tablets debossed with "PRU 2" on one side and no debossing on the other side. They are supplied as:

- NDC 54092-547-01: HDPE bottle of 30 tablets, with child-resistant closure.

STORAGE AND HANDLING

Store MOTEGRITY at 20°C to 25°C (68°F to 77°F); excursions permitted between 15°C to 30°C (between 59°F to 86°F) [see USP Controlled Room Temperature].

Store MOTEGRITY in the original container to protect from moisture.

17 PATIENT COUNSELING INFORMATION

Advise the patient to read the FDA-approved patient labeling (Patient Information).

- Suicidal Ideation and Behavior: Inform patients, their caregivers, and family members that suicidal ideation and behavior, self-injurious ideation as well as new onset or worsening depression have been reported in patients treated with MOTEGRITY. Advise them to be aware of any unusual changes in mood or behavior, new onset or worsening of depression, or the emergence of suicidal thoughts or behavior. Instruct patients, caregivers, and family members to discontinue MOTEGRITY immediately and contact their healthcare provider if any of these symptoms occur [see Warnings and Precautions (5.1)].
- Pregnancy: Advise patients that there is a pregnancy registry that monitors pregnancy outcomes in women exposed to MOTEGRITY during pregnancy [see Use in Specific Populations (8.1)].

Storage

Advise patients to keep MOTEGRITY in the original container to protect from moisture.

Distributed by:
Takeda Pharmaceuticals America, Inc.
Cambridge, MA 02142

For more information go to www.motegrity.com or call 1-800-828-2088

MOTEGRITY and the MOTEGRITY Logo are registered trademarks of Takeda Pharmaceuticals U.S.A., Inc.
TAKEDA and are registered trademarks of Takeda Pharmaceutical Company Limited.
© 2025 Takeda Pharmaceuticals U.S.A., Inc. All rights reserved.

PATIENT INFORMATION
MOTEGRITY® (moe-teh'-gri-tee)
(prucalopride) tablets, for oral use

What is MOTEGRITY?
MOTEGRITY is a prescription medicine used in adults to treat a type of constipation called chronic idiopathic constipation (CIC). Idiopathic means the cause of the constipation is unknown.
It is not known if MOTEGRITY is safe and effective in children.

Do not take MOTEGRITY if you:

- are allergic to MOTEGRITY. Allergic reaction symptoms may include trouble breathing, rash, itching and swelling of your face, lips, tongue or throat.
- have a tear in your stomach or intestinal wall (bowel perforation), a bowel blockage (intestinal obstruction) or serious conditions of the intestinal wall such as Crohn's disease or ulcerative colitis.

Before taking MOTEGRITY, tell your healthcare provider about all of your medical conditions, including if you:

- have or have had depression, suicidal thoughts or actions, or mood problems.
- have kidney problems. Your healthcare provider may give you a lower dose of MOTEGRITY.
- are pregnant or plan to become pregnant. It is not known if MOTEGRITY will harm your unborn baby.
- Pregnancy Registry: There is a pregnancy registry for women who become pregnant during treatment with MOTEGRITY. The purpose of this registry is to collect information about the health of you and your baby. Talk to your healthcare provider about how you can take part in this registry.
- are breastfeeding or plan to breastfeed. Prucalopride can pass into your breastmilk. Talk with your healthcare provider about the best way to feed your baby if you take MOTEGRITY.

Tell your healthcare provider about all the medicines you take, including prescription and over-the-counter medicines, vitamins, and herbal supplements.

How should I take MOTEGRITY?

- Take 1 MOTEGRITY tablet each day or as directed by your healthcare provider.
- Take MOTEGRITY exactly as your healthcare provider tells you to take it.
- Take MOTEGRITY with or without food.

What are the possible side effects of MOTEGRITY?
MOTEGRITY may cause serious side effects, including:

unusual changes in mood or behavior, thoughts of hurting yourself, trying to hurt yourself, or suicide. Stop taking MOTEGRITY right away and tell your healthcare provider immediately if your depression gets worse, you feel sad, hopeless, begin to have thoughts of suicide, thoughts of hurting yourself or you have tried to hurt yourself or if you develop new depression.

The most common side effects of MOTEGRITY include:

- headache
- stomach area (abdominal) pain or bloating

- nausea
- diarrhea

- dizziness
- vomiting

- gas
- fatigue

These are not all the possible side effects of MOTEGRITY.
Call your doctor for medical advice about side effects. You may report side effects to FDA at 1-800-FDA-1088.

How should I store MOTEGRITY?

- Store MOTEGRITY at room temperature between 68°F to 77°F (20°C to 25°C).
- Store MOTEGRITY in the original container to protect from moisture.

Keep MOTEGRITY and all medicines out of the reach of children.

General information about the safe and effective use of MOTEGRITY.
Medicines are sometimes prescribed for purposes other than those listed in a Patient Information leaflet. Do not use MOTEGRITY for a condition for which it was not prescribed. Do not give MOTEGRITY to other people, even if they have the same symptoms that you have. It may harm them. You can ask your pharmacist or healthcare provider for information about MOTEGRITY that is written for health professionals.

What are the ingredients in MOTEGRITY?
Active ingredient: prucalopride
Inactive ingredients: colloidal silicon dioxide, lactose monohydrate, magnesium stearate and microcrystalline cellulose. The coating contains hypromellose, lactose monohydrate, polyethylene glycol 3000, titanium dioxide and triacetin. The 2-mg tablet also contains red iron oxide, yellow iron oxide and FD&C Blue #2.

Distributed by:
Takeda Pharmaceuticals America, Inc.
Cambridge, MA 02142
MOTEGRITY and the MOTEGRITY Logo are registered trademarks of Takeda Pharmaceuticals U.S.A., Inc.
TAKEDA and are registered trademarks of Takeda Pharmaceutical Company Limited.
© 2025 Takeda Pharmaceuticals U.S.A., Inc. All rights reserved.
TRPIL0
For more information, call Takeda Pharmaceuticals at 1-800-828-2088, or go to www.MOTEGRITY.com.

This Patient Information has been approved by the U.S. Food and Drug Administration.

Revised: July 2025

PRINCIPAL DISPLAY PANEL - 1 mg Tablet Bottle Label

Rx Only
NDC 54092-546-01

motegrity®
(prucalopride) tablets

1 mg

Usual Dose: One tablet once daily.
30 Tablets

PRINCIPAL DISPLAY PANEL - 2 mg Tablet Bottle Label

Rx Only
NDC 54092-547-01

motegrity®
(prucalopride) tablets

2 mg

Usual Dose: One tablet once daily.
30 Tablets